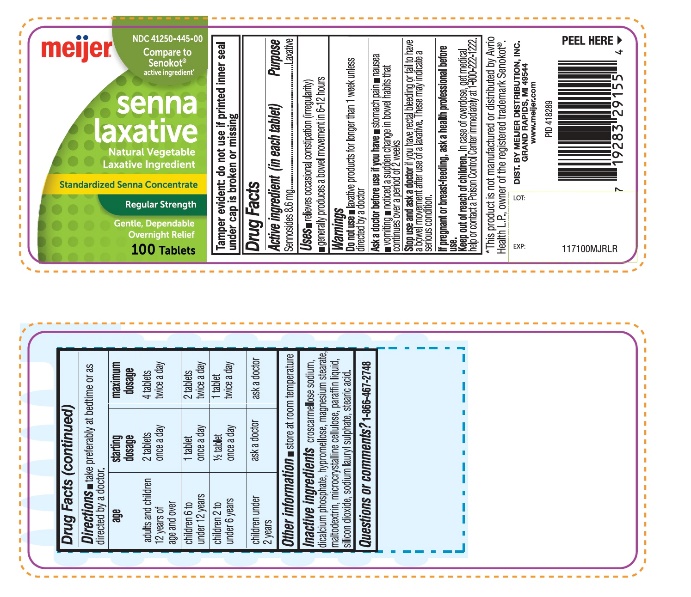 DRUG LABEL: Meijer Senna Laxative

NDC: 41250-445 | Form: TABLET
Manufacturer: MEIJER, INC.
Category: otc | Type: HUMAN OTC DRUG LABEL
Date: 20251024

ACTIVE INGREDIENTS: SENNOSIDES 8.6 mg/1 1
INACTIVE INGREDIENTS: CROSCARMELLOSE SODIUM; ANHYDROUS DIBASIC CALCIUM PHOSPHATE; HYPROMELLOSE, UNSPECIFIED; MAGNESIUM STEARATE; MALTODEXTRIN; MICROCRYSTALLINE CELLULOSE; MINERAL OIL; SILICON DIOXIDE; SODIUM LAURYL SULFATE; STEARIC ACID

Meijer Senna Laxative Standardized Senna Concentrate Drug Facts

Active ingredient (in each tablet)

Sennosides 8.6 mg

Purpose

Laxative

Uses

- relieves occasional constipation (irregularity)
- generally produces a bowel movement within 6- 12 hours.

Warnings

Do not use

- laxative products for longer than 1 week unless directed by a doctor

Ask a doctor before use if you have

- stomach pain
- nausea
- vomiting
- noticed a sudden change in bowel habits that continues over a period of 2 weeks.

Stop use and ask a doctor if

you have rectal bleeding or fail to have a bowel movement after use of a laxative. These may indicate a serious condition.

If pregnant or breast-feeding,

ask a health professional before use.

Keep out of reach of children.

In case of overdose, get medical help or contact a Poison Control Center right immediately at 1-800-222-1222.

Directions

- take preferably at bedtime or as directed by a doctor

age | starting dosage | maximum dosage
adults and children 12 years of age and over | 2 tablets once a day | 4 tablets twice a day
children 6 to under 12 years | 1 tablet once a day | 2 tablets twice a day
children 2 to under 6 years | 1/2 tablet once a day | 1 tablet twice a day
children under 2 years | ask a doctor | ask a doctor

Other information

- store at room temperature

Inactive Ingredients

Croscarmellose sodium, dicalcium phosphate, Hypromellose, maltodextrin, microcrystalline cellulose, magnesium stearate, paraffin liquid, silicon dioxide, sodium lauryl sulphate, stearic acid.

Questions or comments?

Call 1-866-467-2748

Principal Display Panel

NDC# 41250-445-00

*Compare to the active ingredient of Senokot®

Senna Laxative

Standardized Senna Concentrate

Regular Strength

Natural Vegetable Laxative Ingredient

Gentle, dependable

Overnight relief

100 Tablets

*This product is not manufactured or distributed by Avrio Health L.P., owner of the registered trademark Senokot®.

TAMPER EVIDENT: DO NOT USE IF PRINTED SAFETY SEAL UNDER CAP IS BROKEN OR MISSING

DIST. BY MEIJER DISTRIBUTION, INC.

GRAND RAPIDS, MI 49544

www.meijer.com